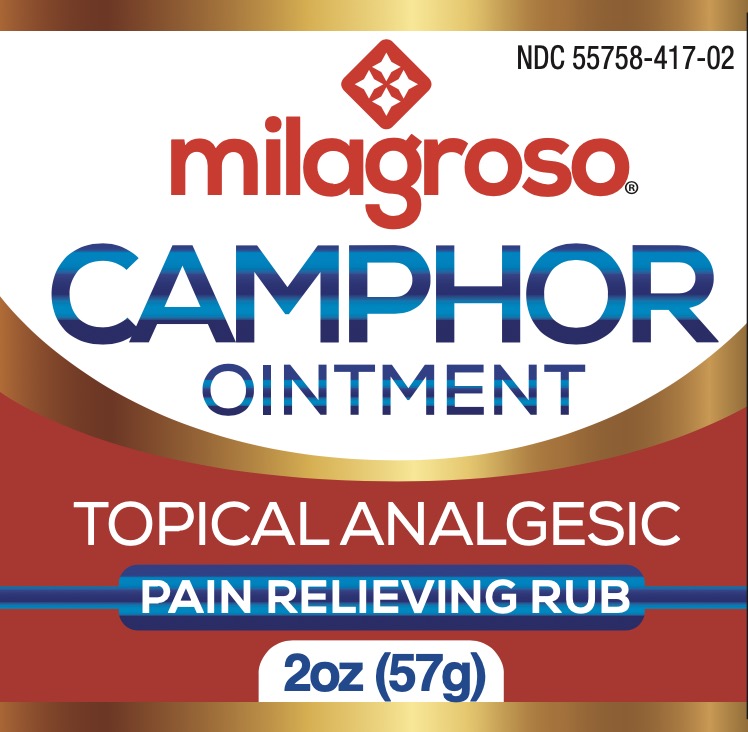 DRUG LABEL: Milagroso
NDC: 55758-417 | Form: OINTMENT
Manufacturer: Pharmadel LLC
Category: otc | Type: HUMAN OTC DRUG LABEL
Date: 20251204

ACTIVE INGREDIENTS: CAMPHOR (SYNTHETIC) 10 g/100 g
INACTIVE INGREDIENTS: PETROLATUM; CYCLOMETHICONE 5

Milagroso Camphor (WP)(DA)

Active ingredient & Purpose

Active ingredient | Purpose
Camphor 10 %............................................................. | Topical analgesic

Uses

For temporary relief of minor aches and pains of muscles and joints associated with

- back aches
- arthritis
- strains
- sprains

Warnings

FOR EXTERNAL USE ONLY. Avoid contact with the eyes .

Do not

- apply to on wounds or damaged skin
- bandage tightly

Stop use and ask a doctor if

- condition worsens or symptoms persist for more than 7 days or clear up and occur again within a few days

If pregnant or breast-feeding,

ask a health professional before use.

Keep out of reach of children.

If swallowed, get medical help or contact a Poison Control Center right away.

Directions

- adults & children 12 years of age and older: apply to affected area not more than 3 to 4 times daily
- children under 2 years of age: consult a doctor

Other information

- store in a cool dry place
- do not use if seal over cap is broken, torn, or missing

Inactive Ingredients

cyclomethicone 5, petrolatum

Questions or Comments?

1-866-359-3478 (M-F) 9 AM to 5 PM EST or www.pharmadel.com

Dist. by:

Pharmadel LLC

Georgetown, DE 19720